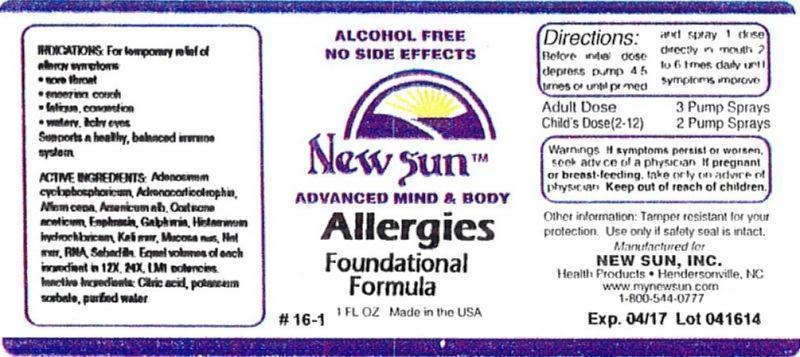 DRUG LABEL: Allergies Foundational Formula
NDC: 66579-0065 | Form: LIQUID
Manufacturer: New Sun Inc.
Category: homeopathic | Type: HUMAN OTC DRUG LABEL
Date: 20140717

ACTIVE INGREDIENTS: ADENOSINE CYCLIC PHOSPHATE 12 [hp_X]/29 mL; CORTICOTROPIN 12 [hp_X]/29 mL; ONION 12 [hp_X]/29 mL; ARSENIC TRIOXIDE 12 [hp_X]/29 mL; CORTISONE ACETATE 12 [hp_X]/29 mL; EUPHRASIA STRICTA 12 [hp_X]/29 mL; GALPHIMIA GLAUCA FLOWERING TOP 12 [hp_X]/29 mL; HISTAMINE DIHYDROCHLORIDE 12 [hp_X]/29 mL; POTASSIUM CHLORIDE 12 [hp_X]/29 mL; SUS SCROFA NASAL MUCOSA 12 [hp_X]/29 mL; SODIUM CHLORIDE 12 [hp_X]/29 mL; SACCHAROMYCES CEREVISIAE RNA 12 [hp_X]/29 mL; SCHOENOCAULON OFFICINALE SEED 12 [hp_X]/29 mL
INACTIVE INGREDIENTS: CITRIC ACID MONOHYDRATE; POTASSIUM SORBATE; WATER

Allergies Foundational Formula

DOSAGE AND ADMINISTRATION

Directions: Before initial dose depress pump 4-5 times or until primed and spray 1 dose directly in mouth 4 to 6 times daily until symptoms improve.

Adult Dose: 3 Pump Sprays

Child's Dose (2-12): 2 Pump Sprays

WARNINGS

Warnings: If symptoms persist or worsen, seek advice of physician. If pregnant or breast-feeding, take only on advice of physician.

Keep out of reach of children.

Other information: Tamper resistant for your protection. Use only if safety seal is intact.

PURPOSE

Indications: For temporary relief of allergy symptoms: •sore throat •sneezing, cough •fatigue, congestion •watery, itchy eyes

Supports a healthy, balanced immune system.

ACTIVE INGREDIENT

Active Ingredients: Adenosinum cyclophosphoricum, Adrenocorticotrophin, Allium cepa, Arsenicum album, Cortisone aceticum, Euphrasia officinalis, Galphimia glauca, Histaminum hydrochloricum, Kali muriaticum, Mucosa nasalis suis, Natrum muriaticum, RNA, Sabadilla. Equal volumes of each ingredient in 12X, 24X, LM1 potencies.

Inactive Ingredient: Citric acid, potassium sorbate, purified water.

Indications: For temporary relief of allergy symptoms:

- sore throat
- sneezing, cough
- fatigue, congestion
- watery, itchy eyes

Supports a healthy, balanced immune system.